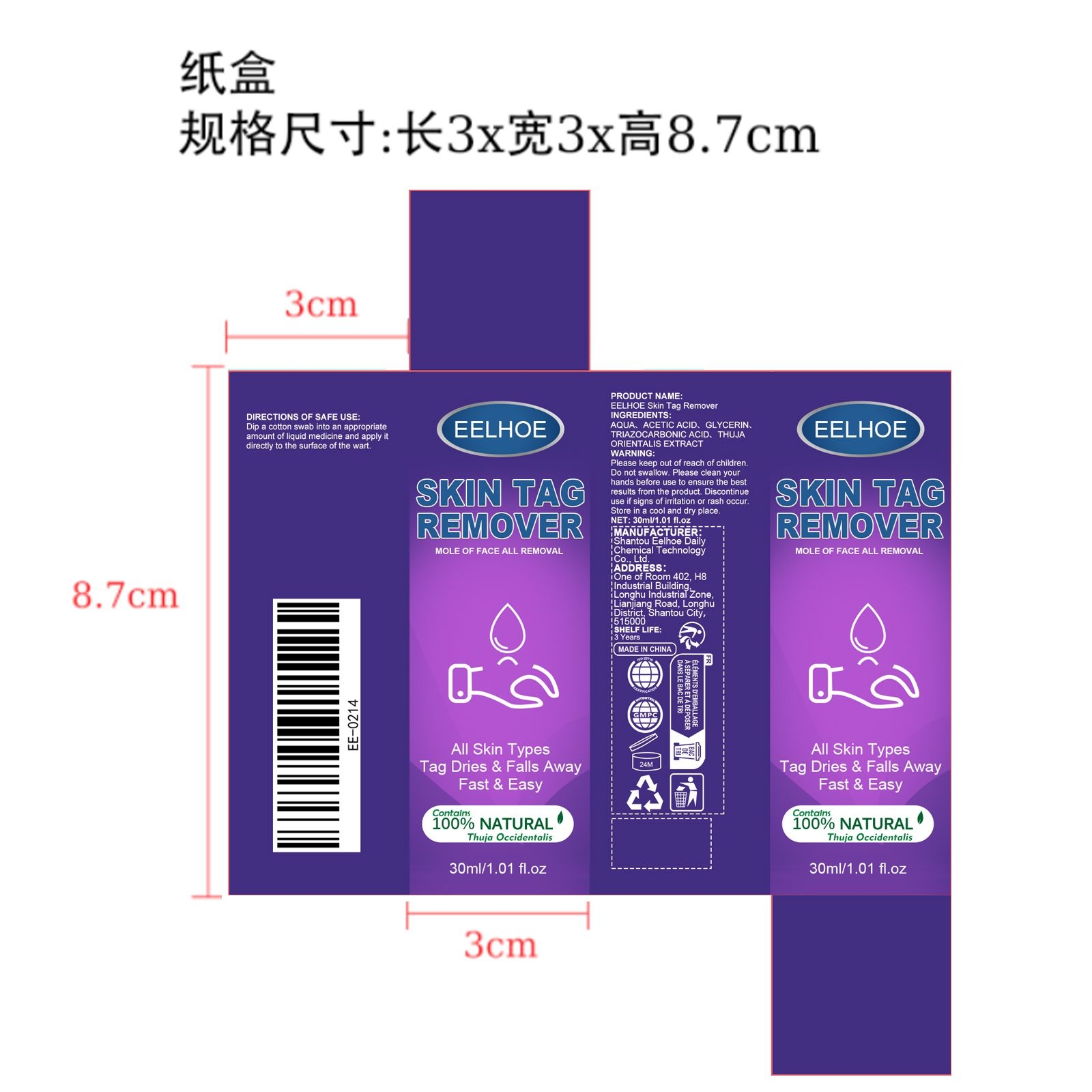 DRUG LABEL: EELHOE Skin Tag Remover
NDC: 85064-007 | Form: LIQUID
Manufacturer: Shantou Eelhoe Daily Chemical Technology Co., Ltd.
Category: otc | Type: HUMAN OTC DRUG LABEL
Date: 20251127

ACTIVE INGREDIENTS: PLATYCLADUS ORIENTALIS LEAF 0.006 mg/30 mg
INACTIVE INGREDIENTS: GLYCERIN 0.6 mg/30 mg; ACETIC ACID 1.5 mg/30 mg; AQUA 27.594 mg/30 mg; 4,4',4''-(1,3,5-TRIAZINE-2,4,6-TRIYLTRIIMINO)TRIS(BENZOIC ACID) 0.3 mg/30 mg

ACTIVE INGREDIENT

PLATYCLADUS ORIENTALIS LEAF

WHEN USING

Dip a cotton swab into an appropriate amount of liquid medicine and apply it directly to the surface of the wart.

PURPOSE

All Skin Types
Tag Dries & Falls Away
Fast & Easy

DO NOT USE

Discontinue use if signs of irritation or rash occur.

STOP USE

Discontinue use if signs of irritation or rash occur.

KEEP OUT OF REACH OF CHILDREN

Please keep out of reach of children. Do not swallow.

WARNINGS

Please keep out of reach of children. Do not swallow.Please clean your hands before use to ensure the best results from the product. Discontinue use if signs of irritation or rash occur. Store in a cool and dry place.

STORAGE AND HANDLING

Store in a cool and dry place.

INACTIVE INGREDIENT

AQUA、ACETIC ACID、GLYCERIN、TRIAZOCARBONIC ACID